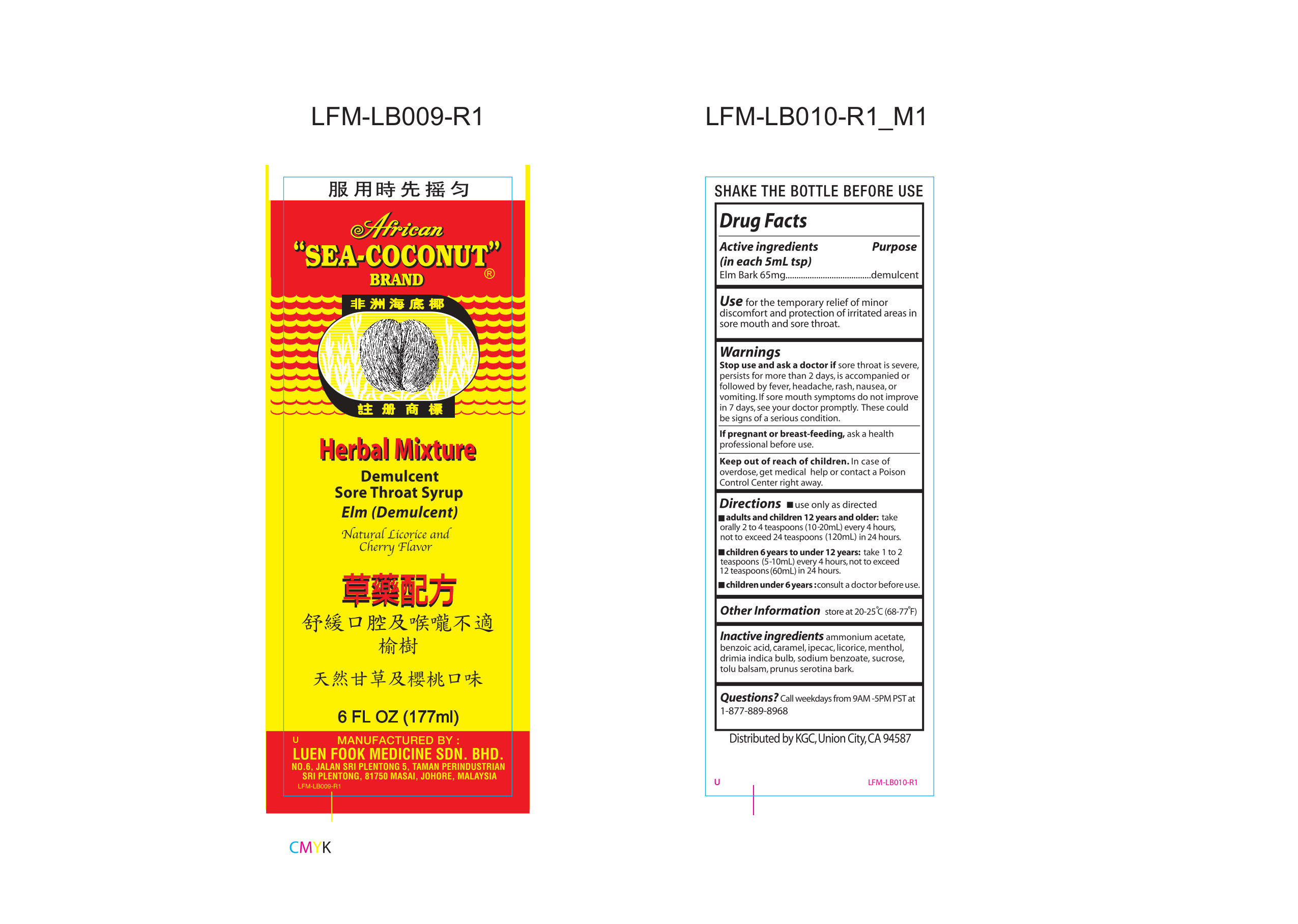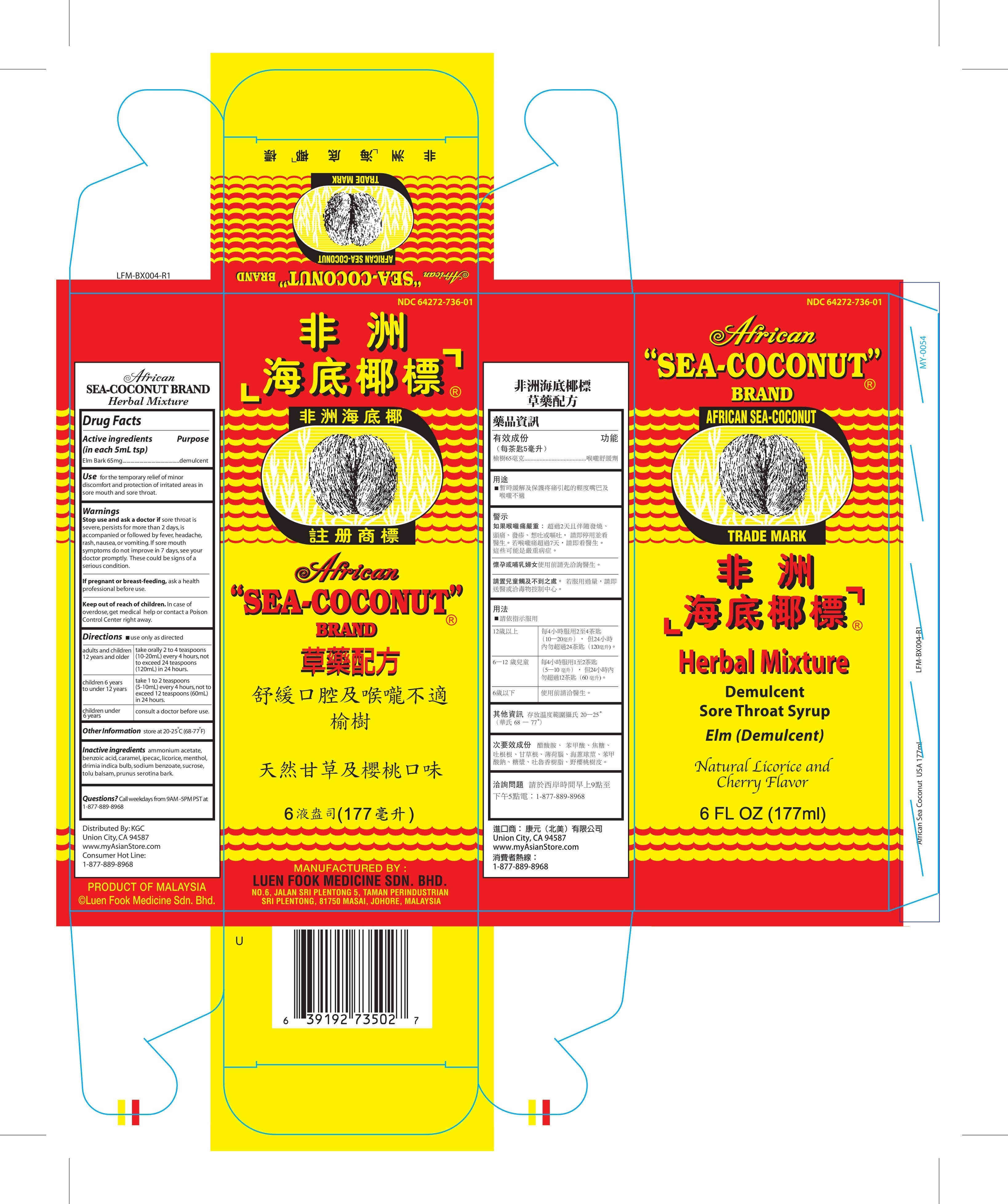 DRUG LABEL: AFRICAN SEA-COCONUT
NDC: 64272-736 | Form: SYRUP
Manufacturer: LUEN FOOK MEDICINE SDN. BHD.
Category: otc | Type: HUMAN OTC DRUG LABEL
Date: 20170626

ACTIVE INGREDIENTS: Elm 65 mg/5 mL
INACTIVE INGREDIENTS: Ammonium Acetate; Benzoic Acid; Caramel; Ipecac; Licorice; Menthol; Drimia Indica Bulb; Sodium Benzoate; Sucrose; Tolu balsam; Prunus Serotina Bark

Drug Facts

Active ingredients (in each 5 mL tsp)

Elm 65 mg

Purpose

Demulcent

Use

for the temporary relief of minor discomfort and protection of irritated areas in sore mouth and sore throat.

Warnings

Stop use and ask a doctor if sore throat is severe, persists for more than 2 days, is accompanied or followed by fever, headache, rash, nausea, or vomiting. If sore mouth symptoms do not improve in 7 days, see your doctor promptly. These could be signs of a serious condition.

PREGNANCY OR BREAST FEEDING

If pregnant or breast-feeding, ask a health professional before use.

Keep out of reach of children. In case of overdose, get medical help or contact a Poison Control Center right away.

Directions

- use only as directed

adults and children 12 years and older | take orally 2 to 4 teaspoons (10-20mL) every 4 hours, not to exceed 24 teaspoons in 24 hours.
children 6 to under 12 years | take 1 to 2 teaspoons (5-10mL) every 4 hours, not to exceed 12 teaspoons in 24 hours.
children under 6 years | consult a doctor before use.

Other Information

store at 20-25∘C (68-77∘F)

Inactive Ingredients

ammonium acetate, benzoic acid, caramel, ipecac, licorice, menthol, drimia Indica bulb, sodium benzoate, sucrose, tolu balsam, prunus serotina bark.

Questions?

Call weekdays from 9 AM-5 PM PST at 1-877-889-8968.

Outer box label

box.jpg

Inner Glass bottle label

bottle.jpg